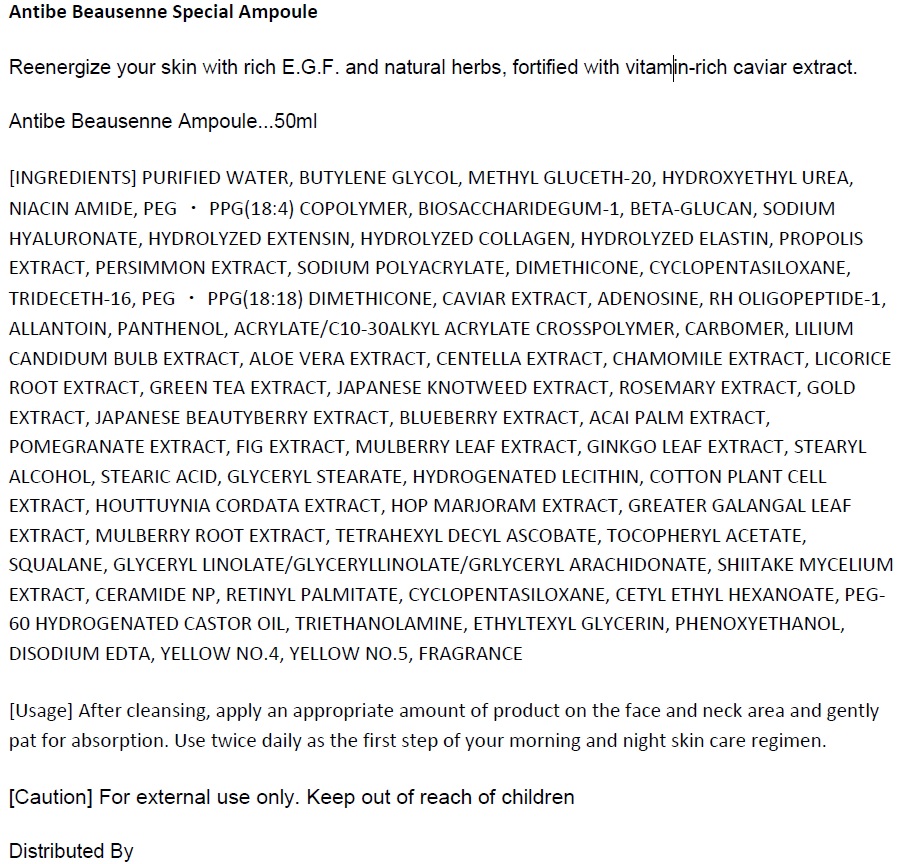 DRUG LABEL: Antibe Beausenne Special Ampoule
NDC: 70929-0002 | Form: GEL
Manufacturer: Modongee Co., Ltd.
Category: otc | Type: HUMAN OTC DRUG LABEL
Date: 20160822

ACTIVE INGREDIENTS: ADENOSINE 0.04 g/100 mL; NIACINAMIDE 2 g/100 mL
INACTIVE INGREDIENTS: WATER; DIMETHICONE; ALLANTOIN

Drug Facts

ACTIVE INGREDIENT

NIACINAMIDE, ADENOSINE

INACTIVE INGREDIENT

PURIFIED WATER, BUTYLENE GLYCOL, METHYL GLUCETH-20, HYDROXYETHYL UREA, PEGㆍPPG(18:4) COPOLYMER, BIOSACCHARIDEGUM-1, BETA-GLUCAN, SODIUM HYALURONATE, HYDROLYZED EXTENSIN, HYDROLYZED COLLAGEN, HYDROLYZED ELASTIN, PROPOLIS EXTRACT, PERSIMMON EXTRACT, SODIUM POLYACRYLATE, DIMETHICONE, CYCLOPENTASILOXANE, TRIDECETH-16, PEGㆍPPG(18:18) DIMETHICONE, CAVIAR EXTRACT, RH OLIGOPEPTIDE-1, ALLANTOIN, PANTHENOL, ACRYLATE/C10-30ALKYL ACRYLATE CROSSPOLYMER, CARBOMER, LILIUM CANDIDUM BULB EXTRACT, ALOE VERA EXTRACT, CENTELLA EXTRACT, CHAMOMILE EXTRACT, LICORICE ROOT EXTRACT, GREEN TEA EXTRACT, JAPANESE KNOTWEED EXTRACT, ROSEMARY EXTRACT, GOLD EXTRACT, JAPANESE BEAUTYBERRY EXTRACT, BLUEBERRY EXTRACT, ACAI PALM EXTRACT, POMEGRANATE EXTRACT, FIG EXTRACT, MULBERRY LEAF EXTRACT, GINKGO LEAF EXTRACT, STEARYL ALCOHOL, STEARIC ACID, GLYCERYL STEARATE, HYDROGENATED LECITHIN, COTTON PLANT CELL EXTRACT, HOUTTUYNIA CORDATA EXTRACT, HOP MARJORAM EXTRACT, GREATER GALANGAL LEAF EXTRACT, MULBERRY ROOT EXTRACT, TETRAHEXYL DECYL ASCOBATE, TOCOPHERYL ACETATE, SQUALANE, GLYCERYL LINOLATE/GLYCERYLLINOLATE/GRLYCERYL ARACHIDONATE, SHIITAKE MYCELIUM EXTRACT, CERAMIDE NP, RETINYL PALMITATE, CYCLOPENTASILOXANE, CETYL ETHYL HEXANOATE, PEG-60 HYDROGENATED CASTOR OIL, TRIETHANOLAMINE, ETHYLTEXYL GLYCERIN, PHENOXYETHANOL, DISODIUM EDTA, YELLOW NO.4, YELLOW NO.5, FRAGRANCE

PURPOSE

Reenergize your skin with rich E.G.F. and natural herbs, fortified with vitamin-rich caviar extract.

keep out or reach of the children

INDICATIONS AND USAGE

After cleansing, apply an appropriate amount of product on the face and neck area and gently pat for absorption. Use twice daily as the first step of your morning and night skin care regimen.

WARNINGS

1. Do not use in the following cases(Eczema and scalp wounds)
2.Side Effects
1)Due to the use of this druf if rash, irritation, itching and symptopms of hypersnesitivity occur dicontinue use and consult your phamacisr or doctor
3.General Precautions
1)If in contact with the eyes, wash out thoroughty with water If the symptoms are servere, seek medical advice immediately
2)This product is for exeternal use only. Do not use for internal use
4.Storage and handling precautions
1)If possible, avoid direct sunlight and store in cool and area of low humidity
2)In order to maintain the quality of the product and avoid misuse
3)Avoid placing the product near fire and store out in reach of children

DOSAGE AND ADMINISTRATION

for external use only